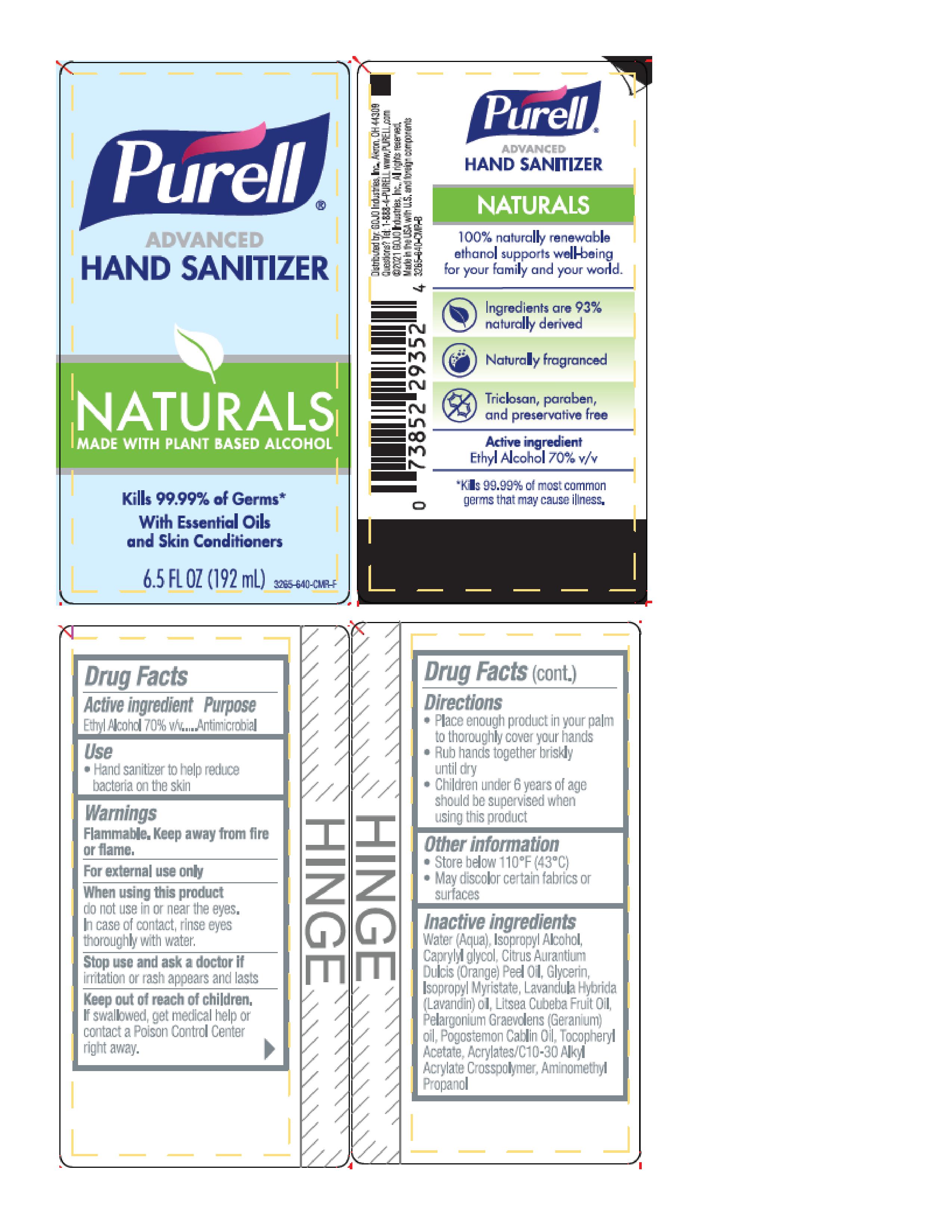 DRUG LABEL: PURELL Advanced Hand Sanitizer Naturals Gel
NDC: 21749-625 | Form: GEL
Manufacturer: GOJO Industries, Inc.
Category: otc | Type: HUMAN OTC DRUG LABEL
Date: 20251210

ACTIVE INGREDIENTS: ALCOHOL 0.7 mL/1 mL
INACTIVE INGREDIENTS: WATER; ISOPROPYL ALCOHOL; CAPRYLYL GLYCOL; CARBOMER INTERPOLYMER TYPE A (ALLYL SUCROSE CROSSLINKED); GLYCERIN; ISOPROPYL MYRISTATE; AMINOMETHYLPROPANOL; BITTER ORANGE OIL; LAVANDIN OIL; LITSEA OIL; GERANIUM OIL, ALGERIAN TYPE; .ALPHA.-TOCOPHEROL ACETATE; PATCHOULI OIL

PURELL Advanced Hand Sanitizer Naturals Gel

Active ingredient

Ethyl alcohol 70% v/v

Purpose

Antimicrobial

Use

Hand sanitizer to help reduce bacteria on the skin

Warnings

Flammable. Keep away from fire or flame.

For external use only

WHEN USING

When using this productdo not use in or near the eyes. In case of contact, rinse eyes thoroughly with water

Stop use and ask a doctor ifirritation or rash appears and lasts

Keep out of reach of children.If swallowed, get medical help or contact a Poison Control Center right away.

Directions

- Put enough product in your palm to cover hands and rub hands together briskly until dry
- Children under 6 yeasr of age should be supervised when using PURELL

Inactive Ingredients:

Water (Aqua), Isopropyl Alcohol, Caprylyl glycol, Citrus Aurantium Dulcis (Orange) Peel Oil, Glycerin, Isopropyl Myristate, Lavandula Hybrida (Lavandin) oil, Litsea Cubeba Fruit Oil, Pelargonium Graevolens (Geranium) oil, Pogostemon Cablin Oil, Tocopheryl Acetate, Acrylates/C10-30 Alkyl Acrylate Crosspolymer, Aminomethyl Propanol